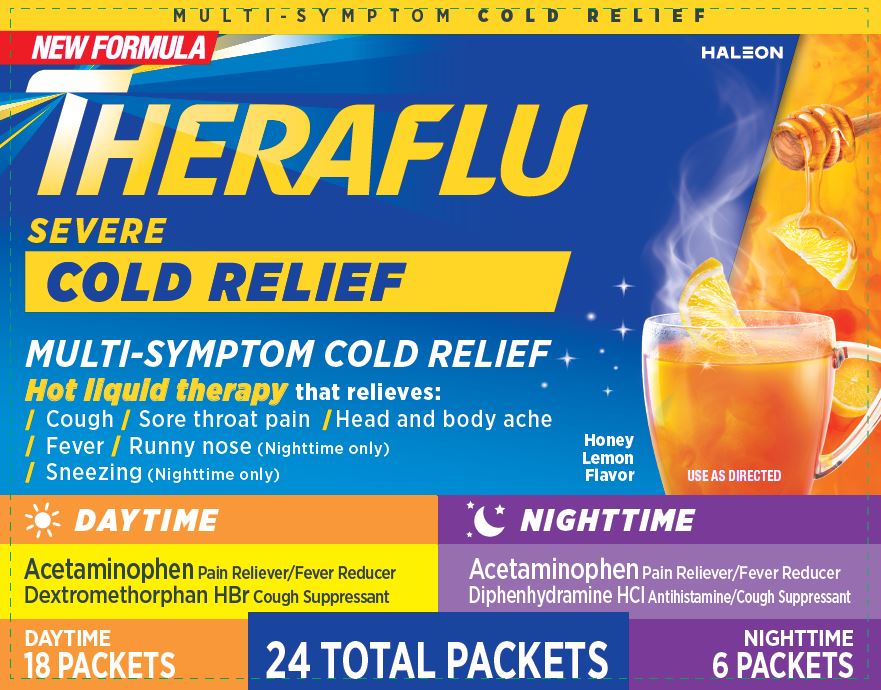 DRUG LABEL: Theraflu
NDC: 0067-0123 | Form: KIT | Route: ORAL
Manufacturer: Haleon US Holdings LLC
Category: otc | Type: HUMAN OTC DRUG LABEL
Date: 20240601

ACTIVE INGREDIENTS: ACETAMINOPHEN 500 mg/1 1; DEXTROMETHORPHAN HYDROBROMIDE 20 mg/1 1; ACETAMINOPHEN 650 mg/1 1; DIPHENHYDRAMINE HYDROCHLORIDE 25 mg/1 1
INACTIVE INGREDIENTS: ACESULFAME POTASSIUM; ANHYDROUS CITRIC ACID; ASPARTAME; D&C YELLOW NO. 10; FD&C BLUE NO. 1; FD&C RED NO. 40; MALTODEXTRIN; SILICON DIOXIDE; SODIUM CITRATE, UNSPECIFIED FORM; SOYBEAN LECITHIN; SUCROSE; TRIBASIC CALCIUM PHOSPHATE; ACESULFAME POTASSIUM; ANHYDROUS CITRIC ACID; ASPARTAME; D&C YELLOW NO. 10; FD&C BLUE NO. 1; FD&C RED NO. 40; MALTODEXTRIN; SILICON DIOXIDE; SODIUM CITRATE, UNSPECIFIED FORM; SOYBEAN LECITHIN; SUCROSE; TRIBASIC CALCIUM PHOSPHATE

Drug Facts

Active Ingredients (in each packet) (Daytime)

Acetaminophen 500 mg

Dextromethorphan HBr 20 mg

Purposes (Daytime)

Pain reliever/Fever reducer

Cough suppressant

Active ingredients (in each packet) (Nighttime)

Acetaminophen 650 mg

Diphenhydramine HCl 25 mg

Purposes (Nighttime)

Pain reliever/Fever reducer

Antihistamine/Cough suppressant

Uses (Daytime)

• temporarily relieves these symptoms due to a cold:

• minor aches and pains • minor sore throat pain • headache
• cough due to minor throat and bronchial irritation

• temporarily reduces fever

Uses (Nighttime)

• temporarily relieves these symptoms due to a cold:

• minor aches and pains • minor sore throat pain
• headache • runny nose
• sneezing • itchy nose or throat
• itchy, watery eyes due to hay fever
• cough due to minor throat and bronchial irritation

• temporarily reduces fever

Warnings (Daytime)

Liver warning: This product contains acetaminophen. Severe liver damage may occur if you take

• more than 4,000 mg of acetaminophen in 24 hours • with other drugs containing acetaminophen

• 3 or more alcoholic drinks every day while using this product

Allergy alert: Acetaminophen may cause severe skin reactions. Symptoms may include:

• skin reddening • blisters • rash

If a skin reaction occurs, stop use and seek medical help right away.

Sore throat warning: If sore throat is severe, persists for more than 2 days, is accompanied or followed by fever, headache, rash, nausea, or vomiting consult a doctor promptly.

Do not use

• in a child under 12 years of age • if you are allergic to acetaminophen

• with any other drug containing acetaminophen (prescription or nonprescription). If you are not sure whether a drug contains acetaminophen, ask a doctor or pharmacist.

• if you are now taking a prescription monoamine oxidase inhibitor (MAOI) (certain drugs for depression, psychiatric, or emotional conditions, or Parkinson’s disease), or for 2 weeks after stopping the MAOI drug. If you do not know if your prescription drug contains an MAOI, ask a doctor or pharmacist before taking this product.

Ask a doctor before use if you have

• liver disease

• cough that occurs with too much phlegm (mucus)

• cough that lasts or is chronic such as occurs with smoking, asthma or emphysema

Ask a doctor or pharmacist before use if you are

• taking the blood thinning drug warfarin

Stop use and ask a doctor if

• fever gets worse or lasts more than 3 days

• redness or swelling is present

• new symptoms occur

• pain or cough gets worse or lasts more than 7 days

• cough comes back or occurs with rash or headache that lasts

These could be signs of a serious condition.

If pregnant or breast-feeding,

ask a health professional before use.

Keep out of reach of children.

In case of overdose, get medical help or contact a Poison Control Center right away. Prompt medical attention is critical for adults as well as for children even if you do not notice any signs or symptoms.

Warnings (Nighttime)

Liver warning: This product contains acetaminophen. Severe liver damage may occur if you take

• more than 4,000 mg of acetaminophen in 24 hours

• with other drugs containing acetaminophen

• 3 or more alcoholic drinks every day while using this product

Allergy alert: Acetaminophen may cause severe skin reactions.

Symptoms may include:

• skin reddening • blisters • rash

If a skin reaction occurs, stop use and seek medical help right away.

Sore throat warning: If sore throat is severe, persists for more than 2 days, is accompanied or followed by fever, headache, rash, nausea, or vomiting consult a doctor promptly.

Do not use

• in a child under 12 years of age

• if you are allergic to acetaminophen

• with any other drug containing acetaminophen (prescription or nonprescription). If you are not sure whether a drug contains acetaminophen, ask a doctor or pharmacist.

• with any other product containing diphenhydramine, even one used on the skin

• if you are now taking a prescription monoamine oxidase inhibitor (MAOI) (certain drugs for depression, psychiatric, or emotional conditions, or Parkinson’s disease), or for 2 weeks after stopping the MAOI drug. If you do not know if your prescription drug contains an MAOI, ask a doctor or pharmacist before taking this product.

Ask a doctor before use if you have

• liver disease • glaucoma

• trouble urinating due to an enlarged prostate gland

• a breathing problem such as emphysema or chronic bronchitis

• cough that occurs with too much phlegm (mucus)

• cough that lasts or is chronic such as occurs with smoking, asthma or emphysema

Ask a doctor or pharmacist before use if you are

• taking sedatives or tranquilizers

• taking the blood thinning drug warfarin

When using this product

• avoid alcoholic drinks

• marked drowsiness may occur

• alcohol, sedatives and tranquilizers may increase drowsiness

• be careful when driving a motor vehicle or operating machinery

• excitability may occur, especially in children

Stop use and ask a doctor if

• fever gets worse or lasts more than 3 days • redness or swelling is present

• new symptoms occur • cough comes back or occurs with rash or headache that lasts

• pain or cough gets worse or lasts more than 7 days

These could be signs of a serious condition.

If pregnant or breast-feeding,

ask a health professional before use.

Keep out of reach of children.

In case of overdose, get medical help or contact a Poison Control Center right away. Prompt medical attention is critical for adults as well as for children even if you do not notice any signs or symptoms.

Directions (Daytime)

• do not use more than directed

• take every 4 hours, while symptoms persist. Do not take more than 6 packets in 24 hours unless directed by a doctor.

Age | Dose
adults and children 12 years of age and over | one packet
children under 12 years of age | do not use

• dissolve contents of one packet into 8 oz. hot water; sip while hot. Consume entire drink within 10-15 minutes.

• if using a microwave, add contents of one packet to 8 oz. of cool water; stir briskly before and after heating. Do not overheat.

Directions (Nighttime)

• do not use more than directed

• take every 4 hours, while symptoms persist. Do not take more than 5 packets in 24 hours unless directed by a doctor.

Age | Dose
adults and children 12 years of age and over | one packet
children under 12 years of age | do not use

• dissolve contents of one packet into 8 oz. hot water; sip while hot. Consume entire drink within 10-15 minutes.

• if using a microwave, add contents of one packet to 8 oz. of cool water; stir briskly before and after heating.

Do not overheat.

Other information (Daytime)

• each packet contains: potassium 10 mg, sodium 20 mg

• phenylketonurics: contains phenylalanine 20 mg per packet

• store at controlled room temperature 20-25°C (68-77°F). Protect product from heat and moisture.

Other information (Nighttime)

• each packet contains: potassium 10 mg, sodium 23 mg

• phenylketonurics: contains phenylalanine 13 mg per packet

• store at controlled room temperature 20-25°C (68-77°F). Protect product from heat and moisture.

Inactive ingredients (Daytime)

acesulfame potassium, anhydrous citric acid, aspartame, D&C yellow no. 10, FD&C blue no. 1, FD&C red no. 40, maltodextrin, natural and artificial flavors, silicon dioxide, sodium citrate, soy lecithin, sucrose, tribasic calcium phosphate

Inactive Ingredients (Nighttime)

acesulfame potassium, anhydrous citric acid, aspartame, D&C yellow no. 10, FD&C blue no. 1, FD&C red no. 40, maltodextrin, natural and artificial flavors, silicon dioxide, sodium citrate, soy lecithin, sucrose, tribasic calcium phosphate

Questions or comments? (Daytime)

1-855-328-5259

Questions or comments? (Nighttime)

1-855-328-5259

Other Information

DO NOT TAKE THE THERAFLU SEVERE COLD RELIEF DAYTIME AND THERAFLU
SEVERE COLD RELIEF NIGHTTIME PRODUCTS AT THE SAME TIME.
DO NOT TAKE MORE THAN 5 DOSES IN TOTAL IN ANY 24 HOUR PERIOD.

PARENTS:
Learn about teen medicine abuse
www.StopMedicineAbuse.org

READ ALL WARNINGS AND DIRECTIONS ON CARTON BEFORE USE.
KEEP CARTON FOR REFERENCE. DO NOT DISCARD.

DO NOT TAKE THE THERAFLU SEVERE COLD RELIEF DAYTIME AND THERAFLU
SEVERE COLD RELIEF NIGHTTIME PRODUCTS AT THE SAME TIME.
DO NOT TAKE MORE THAN 5 DOSES IN TOTAL IN ANY 24 HOUR PERIOD.

DO NOT TAKE A DOSE OF THE SEVERE COLD RELIEF NIGHTTIME PRODUCT
SOONER THAN 4 HOURS AFTER THE LAST DOSE OF SEVERE COLD RELIEF
DAYTIME PRODUCT UNLESS DIRECTED BY YOUR DOCTOR.

TAMPER EVIDENT INNER UNIT
DO NOT USE IF SEALED THERAFLU PACKET IS TORN OR BROKEN

1-855-328-5259

Distributed by: Haleon, Warren, NJ 07059
©2023 Haleon group of companies or its licensor.
Trademarks are owned by or licensed to the Haleon group of companies.
Pat. Info www.productpats.com

207735

Package/Label Principal Display Panel

MULTI-SYMPTOM COLD RELIEF

NEW FORMULA

THERAFLU

SEVERE

COLD RELIEF

MULTI-SYMPTOM COLD RELIEF

Hot liquid therapy that relieves:

/Cough /Sore throat pain /Head and body ache

/Fever /Runny nose (Nighttime only)

/Sneezing (Nighttime only)

Honey Lemon Flavor

USE AS DIRECTED

DAYTIME

Acetaminophen Pain Reliever/Fever Reducer

Dextromethorphan HBr Cough suppressant

NIGHTTIME

Acetaminophen Pain Reliever/Fever Reducer

Diphenhydramine HCl Antihistamine/Cough Suppressant

DAYTIME

18 PACKETS

24 TOTAL PACKETS

NIGHTTIME

6 PACKETS